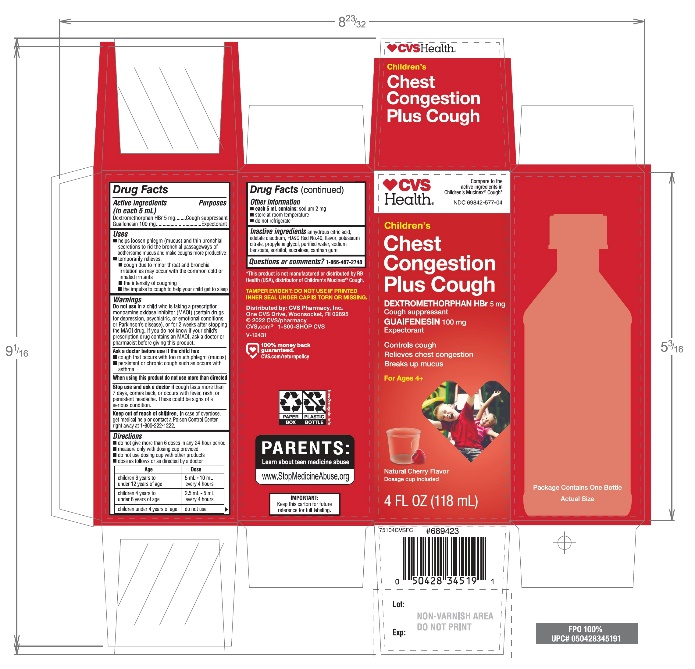 DRUG LABEL: CVS Childrens Cough Relief
NDC: 69842-577 | Form: LIQUID
Manufacturer: CVS PHARMACY, INC
Category: otc | Type: HUMAN OTC DRUG LABEL
Date: 20251210

ACTIVE INGREDIENTS: DEXTROMETHORPHAN HYDROBROMIDE 5 mg/5 mL; GUAIFENESIN 100 mg/5 mL
INACTIVE INGREDIENTS: ANHYDROUS CITRIC ACID; EDETATE SODIUM; FD&C RED NO. 40; POTASSIUM CITRATE; PROPYLENE GLYCOL; WATER; SODIUM BENZOATE; SORBITOL; SUCRALOSE; XANTHAN GUM

CVS Children's Mucus & Cough Relief Cherry Flavor 4FL OZ

Drug Facts

ACTIVE INGREDIENT

Active ingredients (in each 5 mL) | Purpose
Dextromethorphan HBr 5 mg | Cough suppressant
Guaifenesin 100 mg | Expectorant

Uses

- helps loosen phlegm (mucus) and thin bronchial secretions to rid the bronchial passageways of bothersome mucus and make coughs more productive
- temporarily relieves:
  - cough due to minor throat and bronchial irritation as may occur with the common cold or inhaled irritants
  - the intensity of coughing
  - the impulse to cough to help your child get to sleep

Warnings

DO NOT USE

Do not usein a child who is taking a prescription monoamine oxidase inhibitor (MAOI) (certain drugs for depression, psychiatric, or emotional conditions, or Parkinson's disease), or for 2 weeks after stopping the MAOI drug. If you do not know if your child's prescription drug contains an MAOI, ask a doctor or pharmacist before giving this product.

Ask a doctor before use if the child has

- cough that occurs with too much phlegm (mucus)
- persistent or chronic cough such as occurs with asthma

Stop use and ask a doctor ifcough lasts more than 7 days, comes back, or occurs with fever, rash, or persistent headache. These could be signs of a serious condition.

Keep out of reach of children.In case of overdose, get medical help or contact a Poison Control Center right away at 1-800-222-1222.

Directions

- do not take more than 6 doses in any 24-hour period
- measure only with dosing cup provided
- do not use dosing cup with other products
- dose as follows or as directed by a doctor

Age | Dose
children 6 years to under 12 years | 5 mL – 10 mL every 4 hours
children 4 years to under 6 years | 2.5 mL – 5 mL every 4 hours
children under 4 years | do not use

Other information

- each 5 mL contains: sodium 2 mg
- Tamper evident: do not use if printed inner seal under cap is torn or missing
- store at room temperature
- do not refrigerate

Inactive ingredients

anhydrous citric acid, edetate disodium, FD&C red #40, flavors, potassium citrate, propylene glycol, purified water, sodium benzoate, sorbitol, sucralose, xanthan gum

Questions or comments?

1-866-467-2748

PRINCIPAL DISPLAY PANEL - 118 mL Bottle Carton

Compare to the Active Ingredients in Children’s Mucinex®cough

NDC 69842-577-04

Children's Cough Relief

Dextromethorphan HBr , 5 mg

Guaifenesin,100 mg

Natural CherryF lavor

Dosage Cup Included

Ages 4 + years

Controls Cough
Relieves Chest Congestion
Breaks up Mucus

4 FL OZ (118 mL)

*This product is not manufactured or distributed by RB Health (USA), distributor of Children’s Mucinex®Cough.

IMPORTANT: Keep this carton for future reference on full labeling.